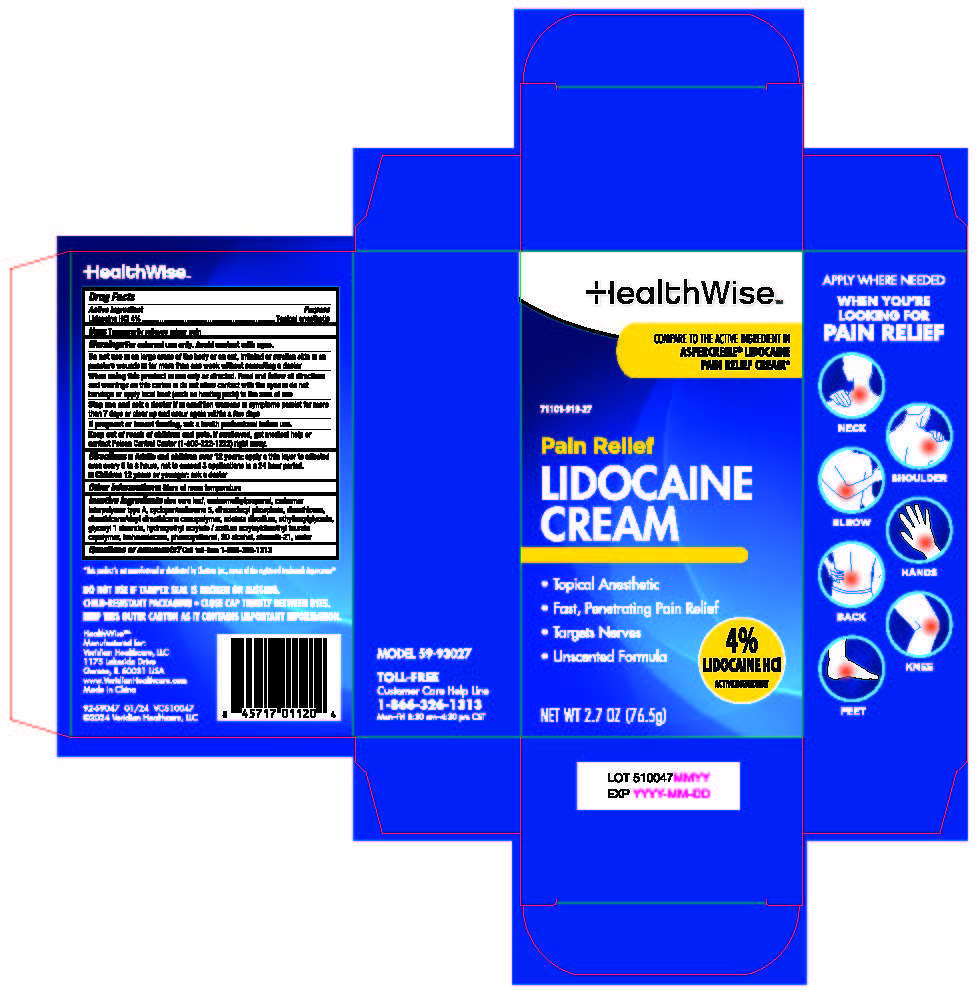 DRUG LABEL: HealthWise 4% Lidocaine Cream
NDC: 71101-919 | Form: CREAM
Manufacturer: Veridian Healthcare	
Category: otc | Type: HUMAN OTC DRUG LABEL
Date: 20241219

ACTIVE INGREDIENTS: LIDOCAINE HYDROCHLORIDE 4 g/100 g
INACTIVE INGREDIENTS: WATER; ALCOHOL; ISOHEXADECANE; HYDROXYETHYL ACRYLATE/SODIUM ACRYLOYLDIMETHYL TAURATE COPOLYMER (45000 MPA.S AT 1%); DIMETHICONE; CYCLOMETHICONE 5; DIHEXADECYL PHOSPHATE; GLYCERYL MONOSTEARATE; ALOE VERA LEAF; DIMETHICONE/VINYL DIMETHICONE CROSSPOLYMER (SOFT PARTICLE); PHENOXYETHANOL; STEARETH-21; AMINOMETHYLPROPANOL; CARBOMER INTERPOLYMER TYPE A (55000 CPS); ETHYLHEXYLGLYCERIN; EDETATE DISODIUM

HealthWise 4% Lidocaine Cream

Active ingredient

Lidocaine HCl 4%

Purpose

Topical anesthetic

Use

temporarily relieves minor pain

Warnings

For external use only. Avoid contact with eyes.

Do not use

- on large areas of the body or on cut, irritated or swollen skin
- on puncture wounds
- for more than one week without consulting a doctor

When using this product

- use only as directed. Read and follow all directions and warnings on this carton.
- do not allow contact with the eyes
- do not bandage or apply local heat (such as heating pads) to the area of use

Stop use and ask a doctor if

- condition worsens
- symptoms persist for more than 7 days or clear up and occur again within a few days

If pregnant or breast-feeding,

ask a health professional before use.

Keep out of reach of children.

If swallowed, get medical help or contact a Poison Control Center (800-222-1222) right away.

Directions

adults and children over 12 years:

- apply a thin layer to affected area every 6 to 8 hours, not to exceed 3 applications in a 24 hour period

children 12 years or younger: ask a doctor

Inactive ingredients

Aloe Vera Leaf, Aminomethylpropanol, Carbomer Interpolymer Type A, Cyclopentasiloxane 5, Dihexadecyl phosphate, Dimethicone, Dimethicone/Vinyl Dimethicone Crosspolymer, edetate disodium, Ethylhexylglycerin, Glyceryl monostearate, Hydroxyethyl Acrylate/ Sodium Acryloyldimethyl Taurate Copolymer, Isohexadecane, Phenoxyethanol, SD Alcohol, Steareth-21, Water